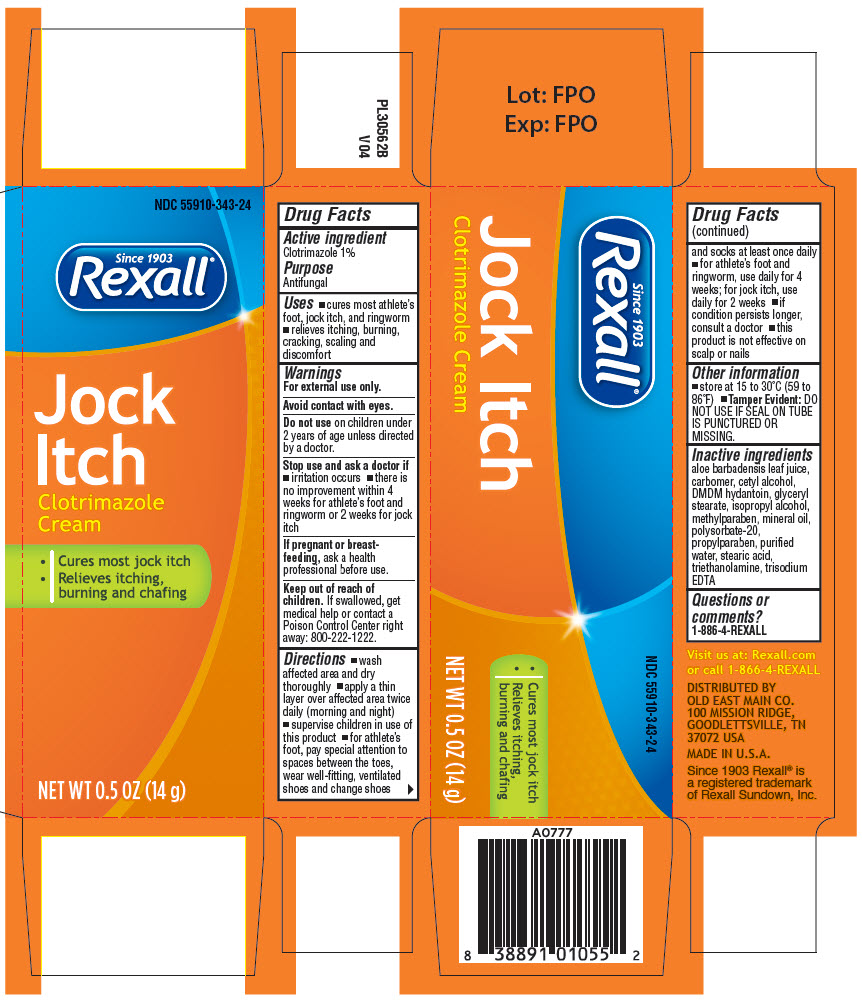 DRUG LABEL: Rexall Jock Itch
NDC: 55910-343 | Form: CREAM
Manufacturer: Dollar General
Category: otc | Type: HUMAN OTC DRUG LABEL
Date: 20250702

ACTIVE INGREDIENTS: CLOTRIMAZOLE 0.01 mg/10 g
INACTIVE INGREDIENTS: ALOE VERA LEAF; CARBOMER HOMOPOLYMER TYPE C (ALLYL PENTAERYTHRITOL CROSSLINKED); CETYL ALCOHOL; DMDM HYDANTOIN; GLYCERYL MONOSTEARATE; isopropyl alcohol; methylparaben; mineral oil; POLYSORBATE 20; propylparaben; WATER; stearic acid; TROLAMINE; EDETATE TRISODIUM

Rexall® Jock Itch
Clotrimazole Cream

Drug Facts

Active ingredient

Clotrimazole 1%

Purpose

Antifungal

Uses

- cures most athlete's foot, jock itch, and ringworm
- relieves itching, burning, cracking, scaling and discomfort

Warnings

For external use only.

Avoid contact with eyes.

Do not use on children under 2 years of age unless directed by a doctor.

Stop use and ask a doctor if

- irritation occurs
- there is no improvement within 4 weeks for athlete's foot and ringworm or 2 weeks for jock itch

PREGNANCY OR BREAST FEEDING

If pregnant or breast-feeding, ask a health professional before use.

Keep out of reach of children. If swallowed, get medical help or contact a Poison Control Center right away: 800-222-1222.

Directions

- wash affected area and dry thoroughly
- apply a thin layer over affected area twice daily (morning and night)
- supervise children in use of this product
- for athlete's foot, pay special attention to spaces between the toes, wear well-fitting, ventilated shoes and change shoes and socks at least once daily
- for athlete's foot and ringworm, use daily for 4 weeks; for jock itch, use daily for 2 weeks
- if condition persists longer, consult a doctor
- this product is not effective on scalp or nails

Other information

- store at 15 to 30°C (59 to 86°F)
- Tamper Evident: DO NOT USE IF SEAL ON TUBE IS PUNCTURED OR MISSING

Inactive ingredients

aloe barbadensis leaf juice, carbomer, cetyl alcohol, DMDM hydantoin, glyceryl stearate, isopropyl alcohol, methylparaben, mineral oil, polysorbate-20, propylparaben, purified water, stearic acid, triethanolamine, trisodium EDTA

Questions or comments?

1-866-4-REXALL

PRINCIPAL DISPLAY PANEL - 14 g Tube Carton

NDC 55910-343-24

Since 1903
Rexall®

Jock
Itch
Clotrimazole
Cream

- Cures most jock itch
- Relieves itching,
  burning and chafing

NET WT 0.5 OZ (14 g)